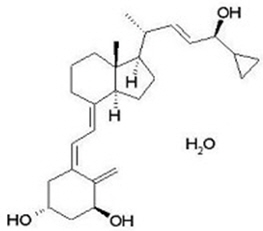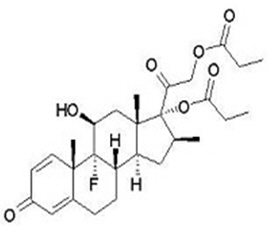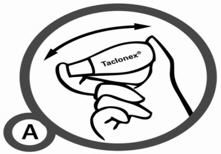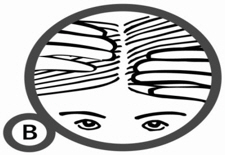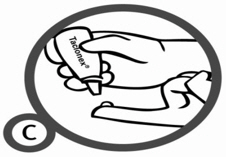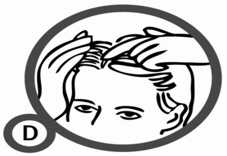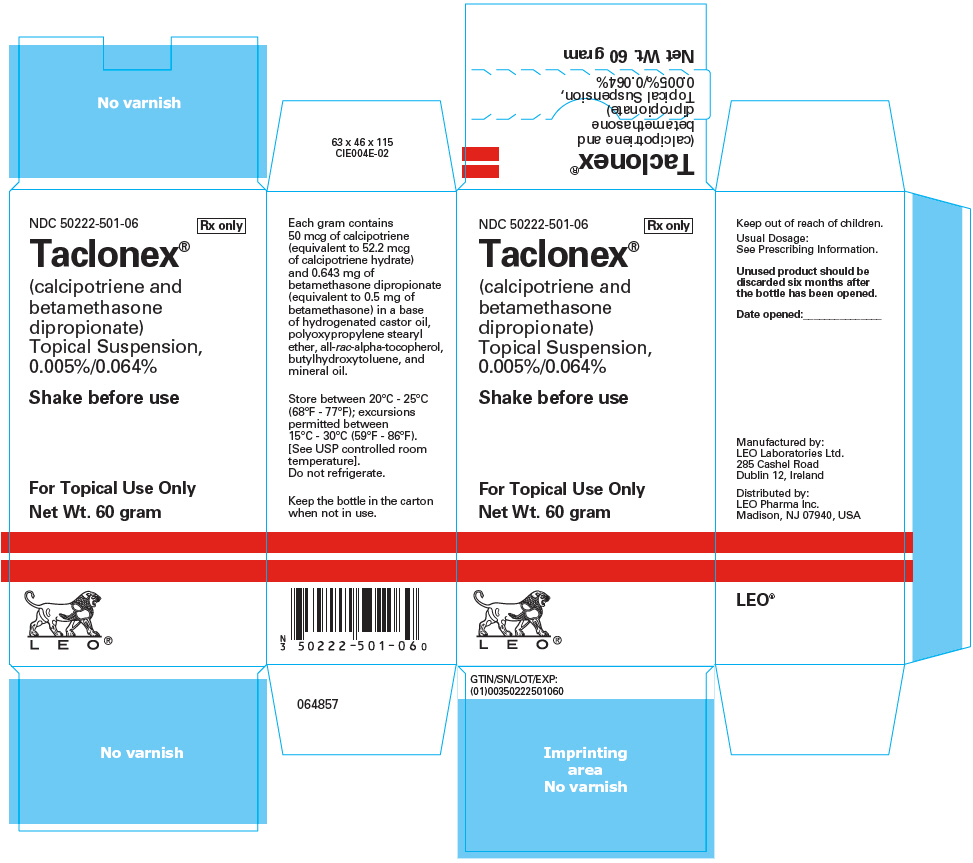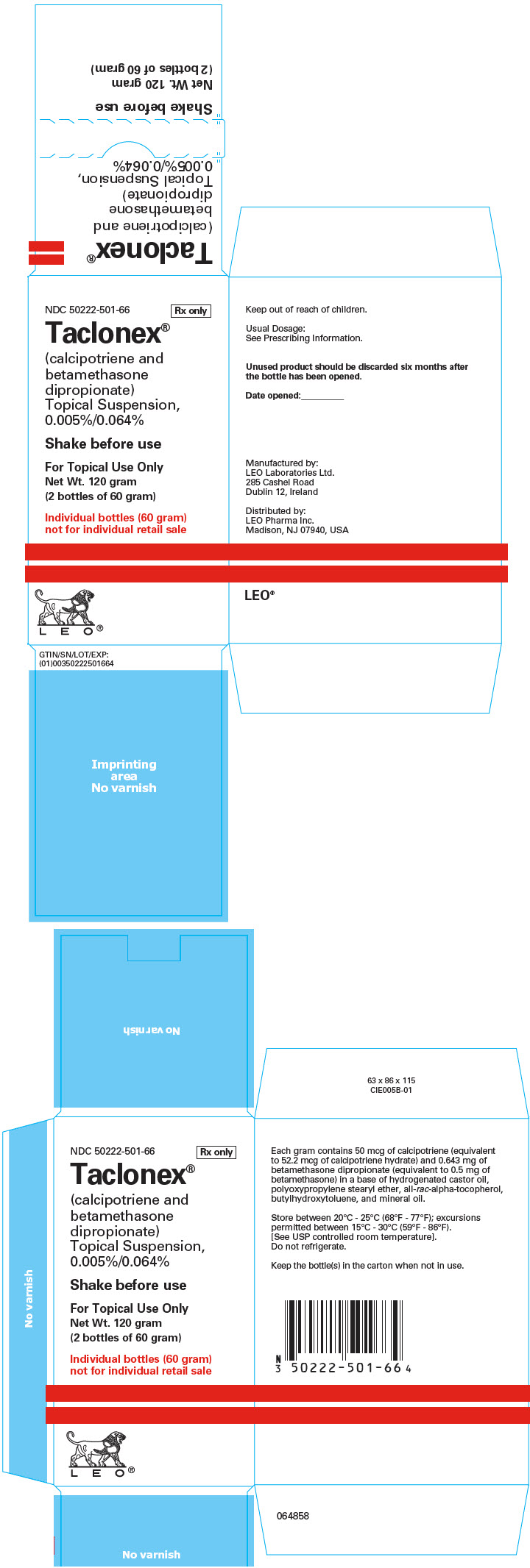 DRUG LABEL: TACLONEX
NDC: 50222-501 | Form: SUSPENSION
Manufacturer: LEO Pharma Inc.
Category: prescription | Type: HUMAN PRESCRIPTION DRUG LABEL
Date: 20171130

ACTIVE INGREDIENTS: CALCIPOTRIENE HYDRATE 50 ug/1 g; BETAMETHASONE DIPROPIONATE 0.5 mg/1 g
INACTIVE INGREDIENTS: HYDROGENATED CASTOR OIL; MINERAL OIL; PPG-11 STEARYL ETHER; .ALPHA.-TOCOPHEROL, DL-; BUTYLATED HYDROXYTOLUENE

HIGHLIGHTS OF PRESCRIBING INFORMATION

These highlights do not include all the information needed to use TACLONEX Topical Suspension safely and effectively. See full prescribing information for TACLONEX Topical Suspension.
TACLONEX® (calcipotriene and betamethasone dipropionate) topical suspension
Initial U.S. Approval: 2006

1 INDICATIONS AND USAGE

Taclonex Topical Suspension is a combination of calcipotriene, a vitamin D analog, and betamethasone dipropionate, a corticosteroid, indicated for the topical treatment of plaque psoriasis of the scalp and body in patients 12 years and older. (1)

2 DOSAGE AND ADMINISTRATION

- Shake bottle before use. (2)
- Apply Taclonex Topical Suspension to affected areas on the scalp and body once daily for up to 8 weeks. Discontinue therapy when control is achieved. (2)
- Patients age 12 to 17 years should not use more than 60 grams per week.(2)
- Adult patients should not use more than 100 grams per week. (2)
- Do not use with occlusive dressings unless directed by a healthcare provider. (2)
- Avoid use on the face, groin, or axillae, or if skin atrophy is present at the treatment site. (2)
- Not for oral, ophthalmic, or intravaginal use. (2)

3 DOSAGE FORMS AND STRENGTHS

Topical Suspension: 0.005%/0.064% - each gram of Taclonex Topical Suspension contains 50 mcg of calcipotriene and 0.643 mg of betamethasone dipropionate. (3)

4 CONTRAINDICATIONS

None. (4)

5 WARNINGS AND PRECAUTIONS

- Hypercalcemia and Hypercalciuria: Hypercalcemia and hypercalciuria have been reported. If either occurs, discontinue until parameters of calcium metabolism normalize. (5.1)
- Effects on Endocrine System: Can cause reversible hypothalamic-pituitary-adrenal (HPA) axis suppression with the potential for glucocorticosteroid insufficiency during and after withdrawal of treatment. Risk factors include the use of high-potency topical corticosteroid, use over a large surface area or to areas under occlusion, prolonged use, altered skin barrier, liver failure, and use in pediatric patients. Modify use should HPA axis suppression develop. (5.2, 8.4)
- Ophthalmic Adverse Reactions: May increase the risk of cataracts and glaucoma. If visual symptoms occur, consider referral to an ophthalmologist. (5.5)

6 ADVERSE REACTIONS

The most common adverse reactions (≥ 1%) are folliculitis and burning sensation of skin. (6.1)

To report SUSPECTED ADVERSE REACTIONS, contact LEO Pharma Inc. at 1-877-494-4536 or FDA at 1-800-FDA-1088 or www.fda.gov/medwatch.

FULL PRESCRIBING INFORMATION

1 INDICATIONS AND USAGE

Taclonex® Topical Suspension is indicated for the topical treatment of plaque psoriasis of the scalp and body in patients 12 years and older.

2 DOSAGE AND ADMINISTRATION

Instruct patients to shake bottle prior to using Taclonex Topical Suspension. Apply Taclonex Topical Suspension to affected areas on the scalp and body once daily for up to 8 weeks. Taclonex Topical Suspension should be discontinued when control is achieved. Instruct patients to wash their hands after applying the product. Inform patients that they should not take a bath or shower or wash their hair right after application of Taclonex Topical Suspension.

Patients 12 to 17 years should not use more than 60 grams per week and patients 18 years and older should not use more than 100 grams per week.

Taclonex Topical Suspension should not be:

- Used with occlusive dressings unless directed by a healthcare provider.
- Used on the face, groin, or axillae, or if skin atrophy is present at the treatment site.
- Applied to the scalp in the 12 hours before or after any chemical treatments to the hair.

Taclonex Topical Suspension is not for oral, ophthalmic, or intravaginal use.

3 DOSAGE FORMS AND STRENGTHS

Topical Suspension: 0.005%/0.064% - each gram contains 50 mcg of calcipotriene and 0.643 mg of betamethasone dipropionate in a viscous, nearly odorless, almost clear, colorless to slightly off-white suspension.

4 CONTRAINDICATIONS

None.

5 WARNINGS AND PRECAUTIONS

5.1 Hypercalcemia and Hypercalciuria

Hypercalcemia and hypercalciuria have been observed with use of Taclonex Topical Suspension. If hypercalcemia or hypercalciuria develop, discontinue treatment until parameters of calcium metabolism have normalized. The incidence of hypercalcemia and hypercalciuria following Taclonex Topical Suspension treatment of more than 8 weeks has not been evaluated [see Clinical Pharmacology (12.2)].

5.2 Effects on Endocrine System

Hypothalamic-Pituitary-Adrenal Axis Suppression

Taclonex Topical Suspension can cause reversible hypothalamic-pituitary-adrenal (HPA) axis suppression with the potential for clinical glucocorticosteroid insufficiency. This may occur during treatment or upon withdrawal of treatment. Factors that predispose a patient to HPA axis suppression include the use of high-potency steroids, large treatment surface areas, prolonged use, use of occlusive dressings, altered skin barrier, liver failure, and young age.

Evaluation for HPA axis suppression may be done by using the adrenocorticotropic hormone (ACTH) stimulation test. If HPA axis suppression is documented, gradually withdraw Taclonex Topical Suspension, reduce the frequency of application, or substitute with a less potent corticosteroid.

The following trials evaluated the effects of Taclonex Topical Suspension on HPA axis suppression:

- In a trial evaluating the effects of Taclonex Topical Suspension and Taclonex Ointment on the HPA axis, 32 adult subjects applied both Taclonex Topical Suspension on the scalp and Taclonex Ointment on the body. Adrenal suppression was identified in 5 of 32 subjects (16%) after 4 weeks of treatment and in 2 of 11 subjects (18%) who continued treatment for 8 weeks. In another trial, 36 adult subjects applied Taclonex Topical Suspension on the body and scalp and 7 subjects applied Taclonex Topical Suspension on the body. Adrenal suppression occurred in 3 out of 43 subjects (7%) after 4 weeks of treatment and in none of the 36 subjects who continued treatment for 8 weeks [see Clinical Pharmacology (12.2)].
- In two trials, the effects of Taclonex Topical Suspension on the HPA axis were evaluated in 31 and 30 pediatric subjects aged 12 to 17 years old who applied Taclonex Topical suspension on the scalp and the scalp/body, respectively. Adrenal suppression occurred in 1 of 30 evaluable subjects (3%) after 4 weeks of treatment (scalp) and 5 of 31 evaluable subjects (16%) after up to 8 weeks of treatment (scalp and body) [see Use in Specific Populations (8.4) and Clinical Pharmacology (12.2)].

Cushing's Syndrome and Hyperglycemia

Cushing's syndrome and hyperglycemia may occur due to the systemic effects of the topical corticosteroid. These complications are rare and generally occur after prolonged exposure to excessively large doses, especially of high-potency topical corticosteroids.

Additional Considerations for Endocrine Adverse Reactions

Pediatric patients may be more susceptible to systemic toxicity due to their larger skin surface to body mass ratios [see Use in Specific Populations (8.4) and Clinical Pharmacology (12.2)].

Use of more than one corticosteroid-containing product at the same time may increase the total systemic corticosteroid exposure.

5.3 Allergic Contact Dermatitis with Topical Corticosteroids

Allergic contact dermatitis to a topical corticosteroid is usually diagnosed by observing a failure to heal rather than a clinical exacerbation. Such an observation should be corroborated with appropriate diagnostic patch testing.

5.4 Allergic Contact Dermatitis with Topical Calcipotriene

Allergic contact dermatitis has been observed with use of topical calcipotriene. Such an observation should be corroborated with appropriate diagnostic patch testing.

5.5 Ophthalmic Adverse Reactions

Use of topical corticosteroids, including Taclonex® Topical Suspension, may increase the risk of posterior subcapsular cataracts and glaucoma. Cataracts and glaucoma have been reported with the postmarketing use of topical corticosteroid products [see Adverse Reactions (6.2)]. Avoid contact of Taclonex Topical Suspension with eyes. Taclonex Topical Suspension may cause eye irritation. Advise patients to report any visual symptoms and consider referral to an ophthalmologist for evaluation.

6 ADVERSE REACTIONS

6.1 Clinical Trials Experience

Because clinical trials are conducted under widely varying conditions, adverse reaction rates observed in the clinical trials of a drug cannot be directly compared to rates in the clinical trials of another drug and may not reflect the rates observed in practice.

Clinical Trials Conducted in Subjects 18 years and older with Psoriasis of the Scalp

The rates of adverse reactions described below were from randomized, multicenter, vehicle- and/or active controlled clinical trials in adult subjects with psoriasis of the scalp [see Clinical Studies (14)]. Subjects applied study product once daily for 8 weeks, and the median weekly dose was 12.6 grams.

Adverse reactions that occurred in ≥1% of subjects treated with Taclonex Topical Suspension and at a rate higher than in subjects treated with vehicle are presented in Table 1.

Table 1. Number and Percentage of Subjects with Adverse Reactions in Scalp Psoriasis Trials (Events Reported by ≥1% of Subjects and for Which a Relationship is Possible)
 | Taclonex Topical Suspension | Betamethasone Dipropionate in vehicle | Calcipotriene in vehicle | Vehicle
 | N=1,953 | N=1,214 | N=979 | N=173
Event | # of subjects (%)
Folliculitis | 16 (1%) | 12 (1%) | 5 (1%) | 0 (0%)
Burning sensation of skin | 13 (1%) | 10 (1%) | 29 (3%) | 0 (0%)

Other less common adverse reactions (<1% but >0.1%) were, in decreasing order of incidence: acne, exacerbation of psoriasis, eye irritation, and pustular rash.

In a 52-week trial, adverse reactions that were reported by >1% of subjects treated with Taclonex Topical Suspension were pruritus (3.6%), psoriasis (2.4%), erythema (2.1%), skin irritation (1.4%), and folliculitis (1.2%).

Clinical Trials Conducted in Subjects 18 years and older with Psoriasis of the Body

In randomized, multicenter, vehicle- and/or active controlled clinical trials in adult subjects with plaque psoriasis on non-scalp areas, 824 subjects applied Taclonex Topical Suspension once daily for 8 weeks [see Clinical Studies (14)]. The median weekly dose was 22.6 grams.

There were no adverse reactions that occurred in ≥1% of subjects treated with Taclonex Topical Suspension and at a rate higher than in subjects treated with vehicle. Other less common adverse reactions (<1% but >0.1%) were, in decreasing order of incidence: rash and folliculitis.

Clinical Trials Conducted in Subjects 12 to 17 years with Psoriasis of the Scalp

In two uncontrolled clinical trials, 109 subjects aged 12 to 17 years with plaque psoriasis of the scalp applied Taclonex® Topical Suspension once daily for up to 8 weeks. The median weekly dose was 40 grams. Adverse reactions included acne, acneiform dermatitis and application site pruritus (0.9% each) [see Use in Specific Populations (8.4) and Clinical Pharmacology (12.2)].

Clinical Trial Conducted in Subjects 12 to 17 years with Psoriasis of the Scalp and Body

In an uncontrolled clinical trial, 107 subjects aged 12 to 17 years with plaque psoriasis of the scalp and body applied Taclonex Topical Suspension once daily for up to 8 weeks. The median weekly dose was 26.6 grams. Adverse reactions were folliculitis, acne, and erythema (0.9% each) [see Use in Specific Populations (8.4) and Clinical Pharmacology (12.2)].

6.2 Postmarketing Experience

Because adverse reactions are reported voluntarily from a population of uncertain size, it is not always possible to reliably estimate their frequency or establish a causal relationship to drug exposure.

Postmarketing reports for local adverse reactions to topical corticosteroids included atrophy, striae, telangiectasias, itching, dryness, hypopigmentation, perioral dermatitis, secondary infection, and miliaria.

Ophthalmic adverse reactions of cataracts, glaucoma, increased intraocular pressure, and central serous chorioretinopathy have been reported during use of topical corticosteroids, including topical betamethasone products.

8 USE IN SPECIFIC POPULATIONS

8.1 Pregnancy

Risk Summary

Available data with Taclonex Topical Suspension are not sufficient to evaluate a drug-associated risk for major birth defects, miscarriages, or adverse maternal or fetal outcomes. Although there are no available data on use of the calcipotriene component in pregnant women, systemic exposure to calcipotriene after topical administration of Taclonex Topical Suspension is likely to be low [see Clinical Pharmacology (12.3)].

Observational studies suggest an increased risk of having low birth weight infants with the maternal use of potent or super potent topical corticosteroids (see Data). Advise pregnant women that Taclonex Topical Suspension may increase the potential risk of having a low birth weight infant and to use Taclonex Topical Suspension on the smallest area of skin and for the shortest duration possible.

In animal reproduction studies, oral administration of calcipotriene to pregnant rats during the period of organogenesis resulted in an increased incidence of minor skeletal abnormalities, including enlarged fontanelles and extra ribs (see Data). Oral administration of calcipotriene to pregnant rabbits during the period of organogenesis had no apparent effects on embryo-fetal development. Subcutaneous administration of betamethasone dipropionate to pregnant rats and rabbits during the period of organogenesis resulted in fetal toxicity, including fetal deaths, reduced fetal weight, and fetal malformations (cleft palate and crooked or short tail) (see Data). The available data do not allow the calculation of relevant comparisons between the systemic exposures of calcipotriene and betamethasone dipropionate observed in animal studies to the systemic exposures that would be expected in humans after topical use of Taclonex Topical Suspension.

The estimated background risk of major birth defects and miscarriage of the indicated population is unknown. All pregnancies have a background risk of birth defect, loss, or other adverse outcomes. In the U.S. general population, the estimated background risk of major birth defects and miscarriage in clinically recognized pregnancies is 2% to 4% and 15% to 20%, respectively.

Data

Human Data

Available observational studies in pregnant women did not identify a drug-associated risk of major birth defects, preterm delivery, or fetal mortality with the use of topical corticosteroids of any potency. However, when the dispensed amount of potent or super potent topical corticosteroids exceeded 300 grams during the entire pregnancy, maternal use was associated with an increased risk of low birth weight in infants.

Animal Data

Embryo-fetal development studies with calcipotriene were performed by the oral route in rats and rabbits. Pregnant rats received dosages of 0, 6, 18, or 54 mcg/kg/day (0, 36, 108, and 324 mcg/m^2/day, respectively) on days 6-15 of gestation (the period of organogenesis). There were no apparent effects on maternal survival, behavior, or body weight gain, no effects on litter parameters, and no effects on the incidence of major malformations in fetuses. Fetuses from dams dosed at 54 mcg/kg/day exhibited a significantly increased incidence of minor skeletal abnormalities, including enlarged fontanelles and extra ribs.

Pregnant rabbits were dosed daily with calcipotriene at exposures of 0, 4, 12, or 36 mcg/kg/day (0, 48, 144, and 432 mcg/m^2/day, respectively) on days 6-18 of gestation (the period of organogenesis). Mean maternal body weight gain was reduced in animals dosed at 12 or 36 mcg/kg/day. The incidence of fetal deaths was increased in the group dosed at 36 mcg/kg/day; reduced fetal weight was also observed in this group. The incidence of major malformations among fetuses was not affected. An increase in the incidence of minor skeletal abnormalities, including incomplete ossification of sternebrae, pubic bones, and forelimb phalanges, was observed in the group dosed at 36 mcg/kg/day.

Embryo-fetal development studies with betamethasone dipropionate were performed via subcutaneous injection in mice and rabbits. Pregnant mice were administered doses of 0, 156, 625, or 2500 mcg/kg/day (0, 468, 1875, and 7500 mcg/m^2/day, respectively) on days 7 through 13 of gestation (the period of organogenesis). Betamethasone dipropionate induced fetal toxicity, including fetal deaths, reduced fetal weight, malformations (increased incidence of the cleft palate and crooked or short tail), and minor skeletal abnormalities (delayed ossification of vertebra and sternebrae). Fetal toxicity was observed at the lowest exposure that was evaluated (156 mcg/kg/day).

Pregnant rabbits were injected subcutaneously at dosages of 0, 0.625, 2.5, and 10 mcg/kg/day (0, 7.5, 30, and 120 mcg/m^2/day, respectively) on days 6 through 18 of gestation (the period of organogenesis). Betamethasone dipropionate induced fetal toxicity, including fetal deaths, reduced fetal weight, external malformations (including malformed ears, cleft palate, umbilical hernia, kinked tail, club foot, and club hand), and skeletal malformations (including absence of phalanges of the first digit and cranial dysplasia) at dosages of 2.5 mcg/kg/day and above.

Calcipotriene was evaluated for effects on peri- and post-natal development when orally administered to pregnant rats at dosages of 0, 6, 18 or 54 mcg/kg/day (0, 36, 108, and 324 mcg/m^2/day, respectively) from gestation day 15 through day 20 postpartum. No remarkable effects were observed on any parameter, including survival, behavior, body weight, litter parameters, or the ability to nurse or rear pups.

Betamethasone dipropionate was evaluated for effects on peri- and post-natal development when orally administered to pregnant rats at dosages of 0, 100, 300, and 1000 mcg/kg/day (0, 600, 1800, and 6000 mcg/m^2/day, respectively) from gestation day 6 through day 20 postpartum. Mean maternal body weight was significantly reduced on gestation day 20 in animals dosed at 300 and 1000 mcg/kg/day. The mean duration of gestation was slightly, but statistically significantly, increased at 100, 300, and 1000 mcg/kg/day. The mean percentage of pups that survived to day 4 was reduced in relation to dosage. On lactation day 5, the percentage of pups with a reflex to right themselves when placed on their back was significantly reduced at 1000 mcg/kg/day. No effects on the ability of pups to learn were observed, and the ability of the offspring of treated rats to reproduce was not affected.

8.2 Lactation

Risk Summary

There is no information regarding the presence of topically administered calcipotriene and betamethasone dipropionate in human milk, the effects on the breastfed infant, or the effects on milk production. Concentrations of calcipotriene in plasma are low after topical administration, and therefore, concentrations in human milk are likely to be low [see Clinical Pharmacology (12.3)]. It is not known whether topical administration of large amounts of betamethasone dipropionate could result in sufficient systemic absorption to produce detectable quantities in human milk (see Clinical Considerations). The developmental and health benefits of breastfeeding should be considered along with the mother's clinical need for Taclonex® Topical Suspension and any potential adverse effects on the breastfed child from Taclonex Topical Suspension or from the underlying maternal condition.

Clinical Considerations

To minimize potential exposure to the breastfed infant via breast milk, use Taclonex Topical Suspension on the smallest area of skin and for the shortest duration possible while breastfeeding. Advise breastfeeding women not to apply Taclonex Topical Suspension directly to the nipple and areola to avoid direct infant exposure [see Use in Specific Populations (8.4)].

8.4 Pediatric Use

The safety and effectiveness of Taclonex Topical Suspension for the treatment of plaque psoriasis of the scalp and body have been established in pediatric patients age 12 to 17 years. The use of Taclonex Topical Suspension for this indication is supported by evidence from adequate and well-controlled trials in adults and from three uncontrolled trials in pediatric subjects that enrolled 109 adolescents with moderate psoriasis of the scalp and 107 adolescents with psoriasis of the scalp and body. After 4 weeks of once daily treatment with Taclonex Topical Suspension, HPA axis suppression was observed in 3% of adolescents with psoriasis of the scalp and 16% of adolescents with psoriasis of the scalp and body. Calcium metabolism was evaluated in 107 adolescents with psoriasis of the scalp and body treated with Taclonex Topical Suspension and no cases of hypercalcemia or clinically relevant changes in urinary calcium were reported [see Warnings and Precautions (5.2), Adverse Reactions (6.1), and Clinical Pharmacology (12.2)].

Because of a higher ratio of skin surface area to body mass, pediatric patients are at a greater risk than adults of systemic toxicity when treated with topical corticosteroids. Pediatric patients are, therefore, also at greater risk of HPA axis suppression and adrenal insufficiency with the use of topical corticosteroids including Taclonex® Topical Suspension [see Clinical Pharmacology (12.2)].

Rare systemic toxicities such as Cushing's syndrome, linear growth retardation, delayed weight gain, and intracranial hypertension have been reported in pediatric patients, especially those with prolonged exposure to large doses of high potency topical corticosteroids. Local adverse reactions including striae have also been reported with use of topical corticosteroids in pediatric patients.

The safety and effectiveness of Taclonex Topical Suspension in pediatric patients less than 12 years of age have not been established.

8.5 Geriatric Use

Clinical studies of Taclonex Topical Suspension in plaque psoriasis on non-scalp areas included 124 subjects who were 65 years of age or older, and 36 were 75 years of age or older. Clinical studies of Taclonex Topical Suspension in subjects with psoriasis of the scalp included 334 subjects who were 65 years or older and 84 subjects who were 75 years or older.

No overall differences in safety or effectiveness of Taclonex Topical Suspension were observed between these subjects and younger subjects, and other reported clinical experience has not identified any differences in responses between the elderly and younger subjects, but greater sensitivity of some older individuals cannot be ruled out.

11 DESCRIPTION

Taclonex Topical Suspension contains calcipotriene hydrate and betamethasone dipropionate. It is for topical use only. Calcipotriene hydrate is a synthetic vitamin D3 analog.

Calcipotriene Hydrate

Calcipotriene hydrate is a vitamin D analog and has the chemical name 9,10-secochola-5,7,10(19),22-tetraene-1,3,24-triol,24-cyclo-propyl-,monohydrate, (1α,3β,5Z,7E,22E,24S) with the empirical formula C27H40O3∙H2O, a molecular weight of 430.6, and the following structural formula (calcipotriene hydrate is a white to almost white, crystalline compound):

Betamethasone Dipropionate

Betamethasone dipropionate is a synthetic corticosteroid and has the chemical name pregna-1,4-diene-3,20-dione-9-fluoro-11-hydroxy-16-methyl-17,21-bis(1-oxypropoxy)-(11β,16β), with the empirical formula C28H37FO7, a molecular weight of 504.6, and the following structural formula (betamethasone dipropionate is a white to almost white, crystalline powder):

Taclonex® Topical Suspension

Each gram of Taclonex Topical Suspension contains 50 mcg of calcipotriene (equivalent to 52.2 mcg of calcipotriene hydrate) and 0.643 mg of betamethasone dipropionate (equivalent to 0.5 mg of betamethasone) in a base of hydrogenated castor oil, polyoxypropylene stearyl ether, all-rac-alpha-tocopherol, butylhydroxytoluene, and mineral oil. Taclonex Topical Suspension is an odorless, clear to slightly off-white suspension.

12 CLINICAL PHARMACOLOGY

12.1 Mechanism of Action

Taclonex Topical Suspension combines the pharmacological effects of calcipotriene hydrate as a synthetic vitamin D3 analog and betamethasone dipropionate as a synthetic corticosteroid. However, while their pharmacologic and clinical effects are known, the exact mechanisms of their actions in the treatment of plaque psoriasis of the scalp and body are unknown.

12.2 Pharmacodynamics

Hypothalamic-Pituitary-Adrenal (HPA) Axis Suppression:

HPA axis suppression was evaluated in four trials (Trial A, B, C, and D) following the application of Taclonex Topical Suspension. In all these trials, adrenal suppression was defined by a 30-minute post-stimulation cortisol level ≤18 mcg/dL.

- In Trial A, HPA axis suppression was evaluated in adult subjects (N=32) with extensive psoriasis involving at least 30% of the scalp and, in total, 15-30% of the body surface area. Treatment consisted of once daily application of Taclonex Topical Suspension on the scalp in combination with Taclonex Ointment on the body for 4 to 8 weeks. Adrenal suppression was observed in 5 of 32 subjects (16%) after 4 weeks of treatment and in 2 of 11 subjects (18%) who continued treatment for 8 weeks.
- In Trial B, HPA axis suppression was evaluated in adult subjects (N=43) with extensive psoriasis involving 15-30% of the body surface area (including the scalp). Treatment consisted of once daily application of Taclonex Topical Suspension to the body (including the scalp in 36 out of 43 subjects) for 4 to 8 weeks. Adrenal suppression was observed in 3 out of 43 subjects (7%) after 4 weeks of treatment and in none of the 36 subjects (0%) who continued treatment for 8 weeks.
- In Trial C, HPA axis suppression was evaluated in pediatric subjects 12 to 17 years (N=30) with plaque psoriasis of the scalp involving at least 20% of the scalp area. Treatment consisted of once daily application of Taclonex Topical Suspension to the affected area on the scalp for up to 8 weeks. Adrenal suppression was observed in 1 of 30 evaluable subjects (3%) after 4 weeks of treatment and in no subjects (0%) who continued treatment for 8 weeks [see Use in Specific Populations (8.4)].
- In Trial D, HPA axis suppression was evaluated in a subset of pediatric subjects aged 12 to 17 years (N=31) with plaque psoriasis of the scalp and body involving 10% to 29% of the body surface area. Adrenal suppression was observed in 5 of 31 subjects (16%): 3 subjects after 4 weeks of treatment, 1 subject after 8 weeks of treatment, and 1 subject after both 4 and 8 weeks of treatment [see Use in Specific Populations (8.4)].

Effects on Calcium Metabolism

The effect on calcium metabolism was evaluated following the application of Taclonex Topical Suspension (these trials are described above).

- In Trial A, elevated urinary calcium levels outside the normal range were observed in two subjects (one at 4 weeks and one at 8 weeks).
- In Trial B, there was no change in mean serum or urinary calcium levels. Elevated urinary calcium levels outside the normal range were observed in two subjects (one at 4 weeks and one at 8 weeks).
- In Trial C (N=109), including 31 subjects with at least 20% scalp involvement and 78 subjects with at least 10% scalp involvement, no cases of hypercalcemia and no clinically relevant changes in urinary calcium were reported.
- In Trial D (N=107), no cases of hypercalcemia and no clinically relevant changes in urinary calcium were reported.

12.3 Pharmacokinetics

Absorption

The systemic effect of Taclonex Topical Suspension in psoriasis was investigated in Trials A, B, and D [see Clinical Pharmacology (12.2)].

In Trial A, the serum levels of calcipotriene and betamethasone dipropionate and their major metabolites were measured after 4 and 8 weeks of once daily application of Taclonex® Topical Suspension on the scalp in combination with Taclonex Ointment on the body. Calcipotriene and betamethasone dipropionate were below the lower limit of quantification in all serum samples of the 34 subjects evaluated. However, one major metabolite of calcipotriene (MC1080) was quantifiable in 10 of 34 (29%) subjects at week 4 and in 5 of 12 (42%) subjects at week 8. The major metabolite of betamethasone dipropionate, betamethasone 17-propionate (B17P) was also quantifiable in 19 of 34 (56%) subjects at week 4 and 7 of 12 (58%) subjects at week 8. The serum concentrations for MC1080 ranged from 20-75 pg/mL. The clinical significance of this finding is unknown.

In Trial B, the plasma levels of calcipotriene and betamethasone dipropionate and their major metabolites were measured after 4 weeks of once daily application of Taclonex Topical Suspension. Calcipotriene and its metabolite MC1080 were below the lower limit of quantification in all plasma samples. Betamethasone dipropionate was quantifiable in 4 of 43 (9) subjects. The metabolite of betamethasone dipropionate (B17P) was quantifiable in 16 of 43 (37%) subjects. The plasma concentrations of betamethasone dipropionate ranged from 30.9-63.5 pg/mL and that of its metabolite betamethasone 17-propionate ranged from 30.5-257 pg/mL. The clinical significance of this finding is unknown.

In Trial D, the plasma levels of calcipotriene and betamethasone dipropionate and their major metabolites were measured after 4 weeks of once daily application of Taclonex Topical Suspension. Calcipotriene and its metabolite MC1080 were below the lower limit of quantification in all plasma samples. Betamethasone dipropionate was quantifiable in 4 of 32 (13%) subjects. The metabolite of betamethasone dipropionate (B17P) was quantifiable in 5 of 32 (16%) subjects. The plasma concentrations of betamethasone dipropionate ranged from 41.4-104 pg/mL and that of its metabolite betamethasone 17-propionate ranged from 30.1-126 pg/mL. The clinical significance of this finding is unknown.

Elimination

Metabolism

Calcipotriene: Calcipotriene metabolism following systemic uptake is rapid and occurs in the liver. The primary metabolites of calcipotriene are less potent than the parent compound.

Calcipotriene is metabolized to MC1046 (the α,β-unsaturated ketone analog of calcipotriene), which is metabolized further to MC1080 (a saturated ketone analog). MC1080 is the major metabolite in plasma. MC1080 is slowly metabolized to calcitroic acid.

Betamethasone dipropionate: Betamethasone dipropionate is metabolized to betamethasone 17-propionate and betamethasone, including the 6β-hydroxy derivatives of those compounds by hydrolysis. Betamethasone 17-propionate (B17P) is the primary metabolite.

13 NONCLINICAL TOXICOLOGY

13.1 Carcinogenesis, Mutagenesis, Impairment of Fertility

When calcipotriene was applied topically to mice for up to 24 months at dosages of 3, 10, and 30 mcg/kg/day (9, 30, and 90 mcg/m^2/day, respectively), no significant changes in tumor incidence were observed when compared to control.

A 104-week oral carcinogenicity study was conducted with calcipotriene in male and female rats at doses of 1, 5 and 15 mcg/kg/day (6, 30, and 90 mcg/m^2/day, respectively). Beginning week 71, the dosage for high-dose animals of both genders was reduced to 10 mcg/kg/day (60 mcg/m^2/day). A treatment-related increase in benign C-cell adenomas was observed in the thyroid of females that received 15 mcg/kg/day. A treatment-related increase in benign pheochromocytomas was observed in the adrenal glands of males that received 15 mcg/kg/day. No other statistically significant differences in tumor incidence were observed when compared to control. The relevance of these findings to patients is unknown.

When betamethasone dipropionate was applied topically to CD-1 mice for up to 24 months at dosages approximating 1.3, 4.2, and 8.5 mcg/kg/day in females, and 1.3, 4.2, and 12.9 mcg/kg/day in males (up to 26 mcg/m^2/day and 39 mcg/m^2/day, in females and males, respectively), no significant changes in tumor incidence were observed when compared to control.

When betamethasone dipropionate was administered via oral gavage to male and female Sprague Dawley rats for up to 24 months at dosages of 20, 60, and 200 mcg/kg/day (120, 360, and 1200 mcg/m^2/day, respectively), no significant changes in tumor incidence were observed when compared to control.

Calcipotriene did not elicit any genotoxic effects in the Ames mutagenicity assay, the mouse lymphoma TK locus assay, the human lymphocyte chromosome aberration test, or the mouse micronucleus test. Betamethasone dipropionate did not elicit any genotoxic effects in the Ames mutagenicity assay, the mouse lymphoma TK locus assay, or in the rat micronucleus test.

Studies in rats with oral doses of up to 54 mcg/kg/day (324 mcg/m^2/day) of calcipotriene indicated no impairment of fertility or general reproductive performance. Studies in male rats at oral doses of up to 200 mcg/kg/day (1200 mcg/m^2/day), and in female rats at oral doses of up to 1000 mcg/kg/day (6000 mcg/m^2/day), of betamethasone dipropionate indicated no impairment of fertility.

14 CLINICAL STUDIES

Clinical Trials Conducted in Subjects 18 Years and Older with Psoriasis of the Scalp

Two multicenter, randomized, double-blind trials were conducted in adult subjects with moderate to very severe psoriasis of the scalp.

- In Trial One, 1,407 subjects were randomized to 1 of 4 treatment groups: Taclonex® Topical Suspension, betamethasone dipropionate in the same vehicle, calcipotriene in the same vehicle, or the vehicle alone.
- In Trial Two, 1,280 subjects were randomized to 1 of 3 treatment groups: Taclonex Topical Suspension, betamethasone dipropionate in the same vehicle, or calcipotriene in the same vehicle.

Both trials enrolled subjects with moderate to very severe psoriasis of the scalp. The majority of subjects had disease of moderate severity at baseline. Subjects were treated once daily for 8 weeks. Efficacy was assessed as the proportion of subjects at Week 8 with absent or very mild disease according to the Investigator's Global Assessment of Disease Severity. "Clear" was defined as no evidence of redness, thickness or scaling. "Almost clear" was defined as an overall clinical picture of lesions with the presence of minimal erythema. Table 2 contains the response rates in each of these 2 trials.

Table 2. Percentage of Subjects with Clear or Almost Clear Disease According to the Investigator's Global Assessment of Disease Severity in Trials on the Scalp
 | Taclonex Topical Suspension | Betamethasone Dipropionate in vehicle | Calcipotriene in vehicle | Vehicle
Trial One | (N=494) | (N=531) | (N=256) | (N=126)
Week 2 | 55.5% | 46.1% | 18.4% | 9.5%
Week 8 | 70.0% | 63.1% | 36.7% | 19.8%
Trial Two | (N=512) | (N=517) | (N=251) | -
Week 2 | 47.1% | 36.4% | 12.7% | -
Week 8 | 67.2% | 59.6% | 41.0% | -

Clinical Trials Conducted in Subjects 18 Years and Older with Psoriasis of the Body

One multicenter, randomized, double-blind trial was conducted in subjects with mild to moderate plaque psoriasis on non-scalp areas, excluding face, axillae, and groin. In this trial, 1152 subjects were randomized to 1 of 4 treatment groups: Taclonex Topical Suspension, betamethasone dipropionate in the same vehicle, calcipotriene in the same vehicle, or the vehicle alone. Seventy eight percent (78%) of subjects had disease of moderate severity at baseline. Subjects were treated once daily for 8 weeks. Efficacy was assessed at Week 4 and Week 8 as the proportion of subjects who were "Clear" or "Almost clear" according to the Investigator's Global Assessment of Disease Severity. Subjects with mild disease at baseline were required to be "Clear" to be considered a success. Table 3 contains the response rates in this trial.

Table 3. Percentage of Subjects with Clear or Almost Clear Disease According to the Investigator's Global Assessment of Disease Severity [Subjects with mild disease at baseline were required to be "Clear" to be considered a success.] in Trial on the Body
 | Taclonex Topical Suspension | Betamethasone Dipropionate in vehicle | Calcipotriene in vehicle | Vehicle
 | (N=482) | (N=479) | (N=96) | (N=95)
Week 4 | 13.3% | 12.5% | 5.2% | 2.1%
Week 8 | 29.0% | 21.5% | 14.6% | 6.3%

16 HOW SUPPLIED/STORAGE AND HANDLING

Taclonex (calcipotriene and betamethasone dipropionate) Topical Suspension, 0.005%/0.064% is a viscous, nearly odorless, almost clear, colorless to slightly off-white suspension. It is available as:

- 60 gram bottle (NDC 50222-501-06)
- 120 gram (2 bottles of 60 gram) (NDC 50222-501-66)

STORAGE AND HANDLING

Store between 20°C - 25°C (68°F - 77°F); excursions permitted between 15°C - 30°C (59°F - 86°F). [See USP controlled room temperature]. Do not refrigerate.

Keep the bottle in the carton when not in use. Unused product should be discarded six months after the bottle has been opened.
Shake before use. Keep out of reach of children.

17 PATIENT COUNSELING INFORMATION

See FDA-approved patient labeling (Patient Information and Instructions for Use).

Administration Instructions

- Instruct pediatric patients (12 to 17 years) not to use more than 60 grams per week.
- Instruct adult patients (18 years and older) not to use more than 100 grams per week.
- Instruct patients to discontinue therapy when control is achieved unless directed otherwise by the healthcare provider.
- Advise patients not to apply Taclonex® Topical Suspension to the scalp in the 12 hours before or after any chemical treatments to the hair since hair treatments may involve strong chemicals. Talk with the healthcare provider first.
- Inform patients that they should not take a bath or shower or wash their hair right after application of Taclonex Topical Suspension.
- Advise patients to avoid use of Taclonex Topical Suspension on the face, underarms, groin or eyes. If this medicine gets on face or in eyes, wash area right away.
- Advise patients not to occlude the treatment area with a bandage or other covering unless directed by the healthcare provider.
- Instruct patients to shake bottle prior to using Taclonex Topical Suspension and to wash hands after application.

Local Reactions and Skin Atrophy

Advise patients that local reactions and skin atrophy are more likely to occur with occlusive use, prolonged use or use of higher potency corticosteroids.

Hypercalcemia and Hypercalciuria

Advise patients that hypercalcemia and hypercalciuria have been observed with the use of Taclonex Topical Suspension [see Warnings and Precautions (5.1)].

HPA Axis Suppression, Cushing's Syndrome, and Hyperglycemia

Advise patients that Taclonex Topical Suspension can cause HPA axis suppression, Cushing's syndrome, and/or hyperglycemia [see Warnings and Precautions (5.2)].

Ophthalmic Adverse Reactions

Advise patients to avoid contact of Taclonex Topical Suspension with eyes and to report any visual symptoms [see Warnings and Precautions (5.5)].

Possible Avoidance of Other Products Containing Calcipotriene or a Corticosteroid

Instruct patients not to use other products containing calcipotriene or a corticosteroid with Taclonex Topical Suspension without first talking to the healthcare provider.

Pregnancy and Lactation

- Advise pregnant women that Taclonex Topical Suspension may increase the potential risk of having a low birth weight infant and to use Taclonex Topical Suspension on the smallest area of skin and for the shortest duration possible [see Use in Specific Populations (8.1)].
- Advise breastfeeding women not to apply Taclonex Topical Suspension directly to the nipple and areola to avoid direct infant exposure [see Use in Specific Populations (8.2)].

Manufactured by: LEO Laboratories Ltd., 285 Cashel Road, Dublin 12, Ireland
Distributed by: LEO Pharma Inc., Madison, NJ 07940, USA

PATIENT INFORMATION
TACLONEX® (TAK-lo-NEKS)
(calcipotriene and betamethasone dipropionate)
Topical Suspension

Important: Taclonex Topical Suspension is for use on skin only (topical). Do not get Taclonex Topical Suspension near or in your mouth, eyes, or vagina.

There are other medicines that contain the same medicine that is in Taclonex Topical Suspension and are used to treat plaque psoriasis. Do not use other products containing calcipotriene or a corticosteroid medicine with Taclonex Topical Suspension without talking to your healthcare provider first.

What is Taclonex Topical Suspension?
Taclonex Topical Suspension is a prescription medicine used on the skin (topical) to treat plaque psoriasis of the scalp and body in people 12 years and older.
It is not known if Taclonex Topical Suspension is safe and effective in children under 12 years of age.

Before you use Taclonex Topical Suspension, tell your healthcare provider about all of your medical conditions, including if you:

- have a calcium metabolism disorder.
- have thinning skin (atrophy) at the treatment site.
- are pregnant or plan to become pregnant. It is not known if Taclonex Topical Suspension will harm your unborn baby. Taclonex Topical Suspension may increase your chance of having a low birth weight baby. If you use Taclonex Topical Suspension during pregnancy, use Taclonex Topical Suspension on the smallest area of the skin and for the shortest time needed.
- are breastfeeding or plan to breastfeed. It is not known if Taclonex Topical Suspension passes into your breast milk. Breastfeeding women should use Taclonex Topical Suspension on the smallest area of the skin and for the shortest time needed. Do not apply Taclonex Topical Suspension directly to the nipple and areola to avoid contact with your baby.

Tell your healthcare provider about all the medicines you take, including prescription and over-the-counter medicines, vitamins, and herbal supplements.

How should I use Taclonex Topical Suspension?
See the "Instructions for Use" for detailed information about the right way to use Taclonex Topical Suspension.

- Use Taclonex Topical Suspension exactly as your healthcare provider tells you to use it.
- Your healthcare provider should tell you how much Taclonex Topical Suspension to use and where to use it.
- Apply Taclonex Topical Suspension to affected areas on the scalp and body 1 time a day for up to 8 weeks. You should stop treatment when your plaque psoriasis is under control, unless your healthcare provider gives you other instructions.
- If you are 12 to 17 years of age, you should not use more than 60 grams of Taclonex Topical Suspension in 1 week.
- If you are 18 years of age or older, you should not use more than 100 grams of Taclonex Topical Suspension in 1 week.
- Do not use Taclonex Topical Suspension longer than prescribed. Using too much Taclonex Topical Suspension, or using it too often, or for too long can increase your risk for having serious side effects.
- Do not apply Taclonex Topical Suspension to the scalp in the 12 hours before or after any chemical treatments to your hair. Since hair treatments may involve strong chemicals, talk with your healthcare provider first.
- Do not use Taclonex Topical Suspension in the mouth, eyes, or vagina.
- Do not use Taclonex Topical Suspension on your face, groin, or armpits, or if you have thinning of your skin (atrophy) at the treatment site.
- If you accidentally get Taclonex Topical Suspension on your face or in your eyes, wash the area with water right away.
- Wash your hands after applying Taclonex Topical Suspension.
- Do not take a bath or shower or wash your hair right after applying Taclonex Topical Suspension as the medicine will not work as well to treat your psoriasis.
- Do not bandage or cover the treated skin area, unless instructed by your healthcare provider.

What are the possible side effects of Taclonex® Topical Suspension?
Taclonex Topical Suspension may cause serious side effects, including:

- Too much calcium in your blood or urine. Your healthcare provider may tell you to stop or temporarily stop treatment with Taclonex Topical Suspension if you have too much calcium in your blood or urine.
- Taclonex Topical Suspension can pass through your skin. Too much Taclonex Topical Suspension passing through your skin can cause your adrenal glands to stop working properly. Your healthcare provider may do blood tests to check for adrenal gland problems.
- Cushing's syndrome, a condition that happens when your body is exposed to large amounts of the hormone cortisol.
- High blood sugar (hyperglycemia).
- Skin problems. Tell your healthcare provider if you have any skin problems, including:

- thinning of your skin
- burning
- inflammation
- itching
- irritation

- dryness
- changes in skin color
- redness
- infection
- raised bumps on your skin

- Eye problems. Using Taclonex Topical Suspension may increase your chance of getting cataracts and glaucoma. Do not get Taclonex Topical Suspension in your eyes because it may cause eye irritation. Tell your healthcare provider if you have blurred vision or other vision problems during treatment with Taclonex Topical Suspension.

The most common side effects of Taclonex Topical Suspension include inflamed hair pores (folliculitis) and skin burning.
Call your doctor for medical advice about side effects. You may report side effects to FDA at 1-800-FDA-1088.

How should I store Taclonex Topical Suspension?

- Store Taclonex Topical Suspension at room temperature between 68°F to 77°F (20°C to 25°C).
- Do not refrigerate Taclonex Topical Suspension.
- Keep the bottle in the carton when not in use.
- Throw away (discard) unused Taclonex Topical Suspension 6 months after it has been opened.

Keep Taclonex Topical Suspension and all medicines out of reach of children.

General information about Taclonex Topical Suspension.
Medicines are sometimes prescribed for purposes other than those listed in a Patient Information leaflet. Do not use Taclonex Topical Suspension for a condition for which it was not prescribed. Do not give Taclonex Topical Suspension to other people, even if they have the same symptoms you have. It may harm them.
You can ask your pharmacist or healthcare provider for information about Taclonex Topical Suspension that is written for health professionals.

What are the ingredients in Taclonex Topical Suspension?
Active ingredients: calcipotriene and betamethasone dipropionate.
Inactive ingredients: hydrogenated castor oil, polyoxypropylene stearyl ether, all-rac-alpha-tocopherol, butylhydroxytoluene and mineral oil.
Manufactured by: LEO Laboratories Ltd., 285 Cashel Road, Dublin 12, Ireland
Distributed by: LEO Pharma Inc., Madison, NJ 07940, USA
For more information, go to www.taclonex.com or call 1-877-494-4536.

This Patient Information has been approved by the U.S. Food and Drug Administration.

Revised: 7/2019

INSTRUCTIONS FOR USE

TACLONEX® (TAK-lo-NEKS)
(calcipotriene and betamethasone dipropionate)
Topical Suspension

Important: Taclonex Topical Suspension is for use on skin only (topical). Do not get Taclonex Topical Suspension near or in your mouth, eyes, or vagina.
Read this Instructions for Use before you start using Taclonex Topical Suspension and each time you get a refill. There may be new information. This information does not take the place of talking with your healthcare provider about your medical condition or treatment.

How to apply Taclonex Topical Suspension to your body:
Follow your healthcare provider's instructions of how much Taclonex Topical Suspension to use and where to use it. Apply Taclonex Topical Suspension directly to areas affected by plaque psoriasis and gently rub in. Wash your hands after applying Taclonex Topical Suspension, unless you are treating areas on your hands.

How to apply Taclonex Topical Suspension to your scalp:
You do not need to wash your hair before you apply Taclonex Topical Suspension.

Step 1: Shake the bottle before use. Remove the cap from the bottle. (See Figure A).

Step 2: Locate the area to treat using your fingers and part your hair. (See Figure B).

Step 3: Squeeze a drop of Taclonex Topical Suspension to your fingertip. (See Figure C).

Step 4: Use your fingers to apply the drop of Taclonex Topical Suspension directly to scalp affected by plaque psoriasis. Gently rub in. (See Figure D).

Step 5: After applying Taclonex Topical Suspension, put the cap back on the bottle.
Step 6: Wash your hands after applying Taclonex Topical Suspension. Do not wash your hair right after you apply Taclonex Topical Suspension to your scalp.

How should I store Taclonex® Topical Suspension?

- Store the Taclonex Topical Suspension at room temperature between 68°F to 77°F (20°C to 25°C).
- Do not refrigerate Taclonex Topical Suspension.
- Keep bottle in the carton when not in use.
- Discard unused Taclonex Topical Suspension 6 months after it has been opened.

Keep Taclonex Topical Suspension and all medicines out of reach of children.

This Instructions for Use has been approved by the U.S. Food and Drug Administration.

Manufactured by:
LEO Laboratories Ltd.
285 Cashel Road
Dublin 12, Ireland

Distributed by:
LEO Pharma Inc.
Madison, NJ 07940, USA

Revised: 7/2019

PRINCIPAL DISPLAY PANEL - 60 g Carton - NDC 50222-501-06

NDC 50222-501-06

Rx only

Taclonex®

(calcipotriene and
betamethasone
dipropionate)
Topical Suspension,
0.005%/0.064%

Shake before use

For Topical Use Only

Net Wt. 60 gram

LEO®

PRINCIPAL DISPLAY PANEL - 120 g Carton - NDC 50222-501-66

NDC 50222-501-66

Rx only

Taclonex®

(calcipotriene and
betamethasone
dipropionate)
Topical Suspension,
0.005%/0.064%

Shake before use

For Topical Use Only
Net Wt. 120 gram
(2 bottles of 60 gram)

Individual bottles (60 gram)
not for individual retail sale

LEO®